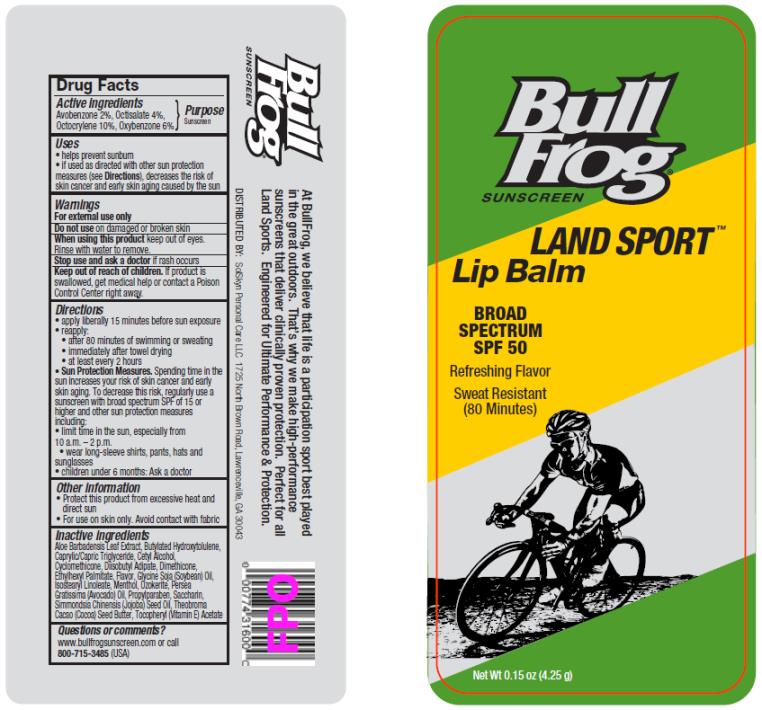 DRUG LABEL: BullFrog Land Sport SPF 50 Lip Balm
NDC: 70281-339 | Form: STICK
Manufacturer: SolSkyn Personal Care LLC
Category: otc | Type: HUMAN OTC DRUG LABEL
Date: 20170816

ACTIVE INGREDIENTS: AVOBENZONE 2 g/100 g; OCTISALATE 4 g/100 g; OCTOCRYLENE 10 g/100 g; OXYBENZONE 6 g/100 g
INACTIVE INGREDIENTS: ALOE VERA LEAF; BUTYLATED HYDROXYTOLUENE; CETYL ALCOHOL; CYCLOMETHICONE; DIISOBUTYL ADIPATE; DIMETHICONE; ETHYLHEXYL PALMITATE; SOYBEAN OIL; ISOSTEARYL LINOLEATE; MENTHOL; CERESIN; AVOCADO OIL; PROPYLPARABEN; SACCHARIN; JOJOBA OIL; COCOA BUTTER; .ALPHA.-TOCOPHEROL SUCCINATE, D-

BullFrog Land Sport Lip SPF50

BullFrog Land Sport SPF 50 Lip Balm

Active Ingredients

Avobenzone 2%, Octisalate 4%, Octocrylene 10%, Oxybenzone 6%

Purpose

Sunscreen

Uses

• helps prevent sunburn

• if used as directed with other sun protection measures (see Directions), decreases the risk of skin cancer and early skin aging caused by the sun

Warnings

• For external use only

• Do not use

on damaged or broken skin.

• When using this product

keep out of eyes. Rinse with water to remove.

• Keep out of reach of children.

If product is swallowed, get medical help or contact a Poison Control Center right away.

Directions

• apply liberally 15 minutes before sun exposure

• re-apply:

• after 80 minutes of swimming or sweating

• immediately after towel drying

• at least every 2 hours

Sun Protection Measures. Spending time in the sun increases your risk of skin cancer and early skin aging. To decrease this risk, regularly use a sunscreen with broad spectrum SPF of 15 or higher and other sun protection measures including:

• limit time in the sun, especially from 10 a.m.-2 p.m.

• wear long-sleeved shirts, pants, hats and sunglasses

• children under 6 months: ask a doctor

Other information

• protect this product from excessive heat and direct sun

• for use on skin only. Avoid contact with fabric

Inactive Ingredients

Aloe Barbadensis Leaf Extract, Butylated Hydroxytolulene, Caprylic/Capric Triglyceride, Cetyl Alcohol, Cyclomethicone, Diisobutyl Adipate, Dimethicone, Ethylhexyl Palmitate, Flavor, Glycine Soja (Soybean) Oil, Isostearyl Linoleate, Menthol, Ozokerite, Persea Gratissima (Avocado) Oil, Propylparaben, Saccharin, Simmondsia Chinensis (Jojoba) Seed Oil, Theobroma Cacao (Cocoa) Seed Butter, Tocopheryl (Vitamin E) Acetate

Questions or comments?

www.bullfrogsunscreen.com or call 1-800-715-3485 (USA)

PRINCIPAL DISPLAY PANEL

Bull Frog
Sunscreen
LAND SPORT
Lip Balm
SPF 50